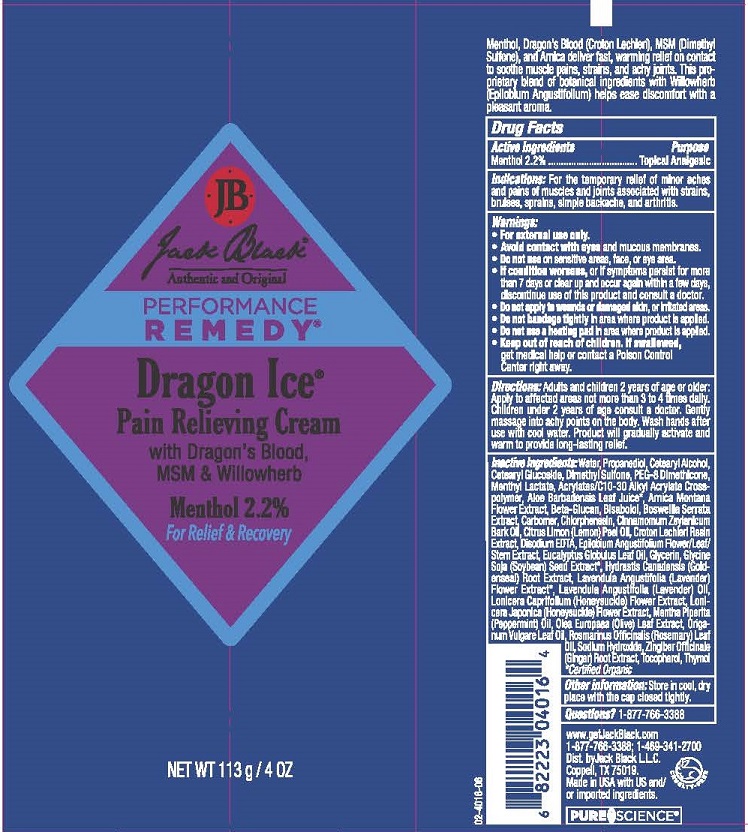 DRUG LABEL: JACK BLACK PERFORMANCE REMEDY DRAGON ICE
NDC: 66738-101 | Form: CREAM
Manufacturer: JACK BLACK LLC
Category: otc | Type: HUMAN OTC DRUG LABEL
Date: 20220103

ACTIVE INGREDIENTS: MENTHOL 2.2 g/100 g
INACTIVE INGREDIENTS: WATER; PROPANEDIOL; CETOSTEARYL ALCOHOL; CETEARYL GLUCOSIDE; DIMETHYL SULFONE; PEG-8 DIMETHICONE; MENTHYL LACTATE, (-)-; CARBOMER INTERPOLYMER TYPE A (ALLYL SUCROSE CROSSLINKED); ALOE VERA LEAF; ARNICA MONTANA; CURDLAN; .ALPHA.-BISABOLOL, (+)-; BOSWELLIA SERRATA WHOLE; CARBOMER HOMOPOLYMER TYPE C (ALLYL PENTAERYTHRITOL CROSSLINKED); CHLORPHENESIN; CINNAMON BARK OIL; LEMON OIL; CROTON LECHLERI RESIN; EDETATE DISODIUM; EPILOBIUM ANGUSTIFOLIUM WHOLE; EUCALYPTUS OIL; SOYBEAN; GOLDENSEAL; LAVANDULA ANGUSTIFOLIA SUBSP. ANGUSTIFOLIA FLOWER; LONICERA CAPRIFOLIUM FLOWER; LONICERA JAPONICA TOP; PEPPERMINT OIL; OLEA EUROPAEA LEAF; OREGANO LEAF OIL; ROSEMARY OIL; SODIUM HYDROXIDE; GINGER; TOCOPHEROL; THYMOL

JACK BLACK - PERFORMANCE REMEDY DRAGON ICE (66738-101)

ACTIVE INGREDIENT

MENTHOL 2.2%

PURPOSE

TOPICAL ANALGESIC

INDICATIONS

FOR THE TEMPORARY RELIEF OF MINOR ACHES AND PAINS OF MUSCLES AND JOINTS ASSOCIATED WITH STRAINS, BRUISES, SPRAINS, SIMPLE BACKACHE, AND ARTHRITIS.

WARNINGS

- FOR EXTERNAL USE ONLY.
- AVOID CONTACT WITH EYES AND MUCOUS MEMBRANES.
- DO NOT USE ON SENSITIVE AREAS, FACE, OR EYE AREA.
- IF CONDITION WORSENS, OR IF SYMPTOMS PERSIST FOR MORE THAN 7 DAYS OR CLEAR UP AND OCCUR AGAIN WITHIN A FEW DAYS, DISCONTINUE USE OF THIS PRODUCT AND CONSULT A DOCTOR.
- DO NOT APPLY TO WOUNDS OR DAMAGED SKIN, OR IRRITATED AREAS.
- DO NOT BANDAGE TIGHTLY IN THE AREA WHERE PRODUCT IS APPLIED.
- DO NOT USE A HEATING PAD IN AREA WHERE PRODUCT IS APPLIED.

KEEP OUT OF REACH OF CHILDREN. IF SWALLOWED, GET MEDICAL HELP OR CONTACT A POISON CONTROL CENTER RIGHT AWAY.

DIRECTIONS

ADULTS AND CHILDREN 2 YEARS OF AGE OR OLDER: APPLY TO AFFECTED AREAS NOT MORE THAN 3 TO 4 TIMES DAILY. CHILDREN UNDER2 YEARS OF AGE CONSULT A DOCTOR. GENTLY MASSAGE INTO ACHY POINTS ON THE BODY. WASH HANDS AFTER USE WITH COOL WATER. PRODUCT WILL GRADUALLY ACTIVATE AND WARM TO PROVIDE LONG-LASTING RELIEF.

INACTIVE INGREDIENTS

WATER, PROPANEDIOL, CETEARYL ALCOHOL, CETEARYL GLUCOSIDE, DIMETHYL SULFONE, PEG-8 DIMETHICONE, MENTHYL LACTATE, ACTYLATES/C10-30 ACRYLATE CROSSPOLYMER, ALOE BARBADENSIS LEAF JUICE*, ARNICA MONTANA FLOWER EXTRACT, BETA-GLUCAN, BISABOLOL, BOSWELLIA SERRATA EXTRACT, CARBOMER, CHLORPHENESIN, CINNAMOMUM ZEYLANICUM BARK OIL, CITRUS LIMON (LEMON) PEEL OIL, CROTON LECHLERI RESIN EXTRACT, DISODIUM EDTA, EPILOBUM ANGUSTIFOLIUM FLOWER/LEAF/STEM EXTRACT, EUCALYPTUS GLOBULUS LEAF OIL, GLYCERIN, GLYCINE SOJA (SOYBEAN) SEED EXTRACT*, HYDRASTIS CANADENSIS (GOLDENSEAL) ROOT EXTRACT, LAVENDULA ANGUSTIFOLIA (LAVENDER) FLOWER EXTRACT*, LAVENDULA ANGUSTIFOLIA (LAVENDER) OIL, LONICERA CAPRIFOLIUM (HONEYSUCKLE) FLOWER EXTRACT, LONICERA JAPONICA (HONEYSUCKLE) FLOWER EXTRACT, MENTHA PIPERITA (PEPPERMINT) OIL, OLEA EUROPAEA (OLIVE) LEAF EXTRACT, ORIGANUM VULGARE LEAF OIL, ROSMARINUS OFFICINALIS (ROSEMARY) LEAF OIL, SODIUM HYDROXIDE, ZINGIBER OFFICINALE (GINGER) ROOT EXTRACT, TOCOPHEROL, THYMOL

*CERTIFIED ORGANIC

OTHER INFORMATION

STORE IN COOL, DRY PLACE WITH CAP CLOSED TIGHTLY.

QUESTIONS?

1-877-766-3388